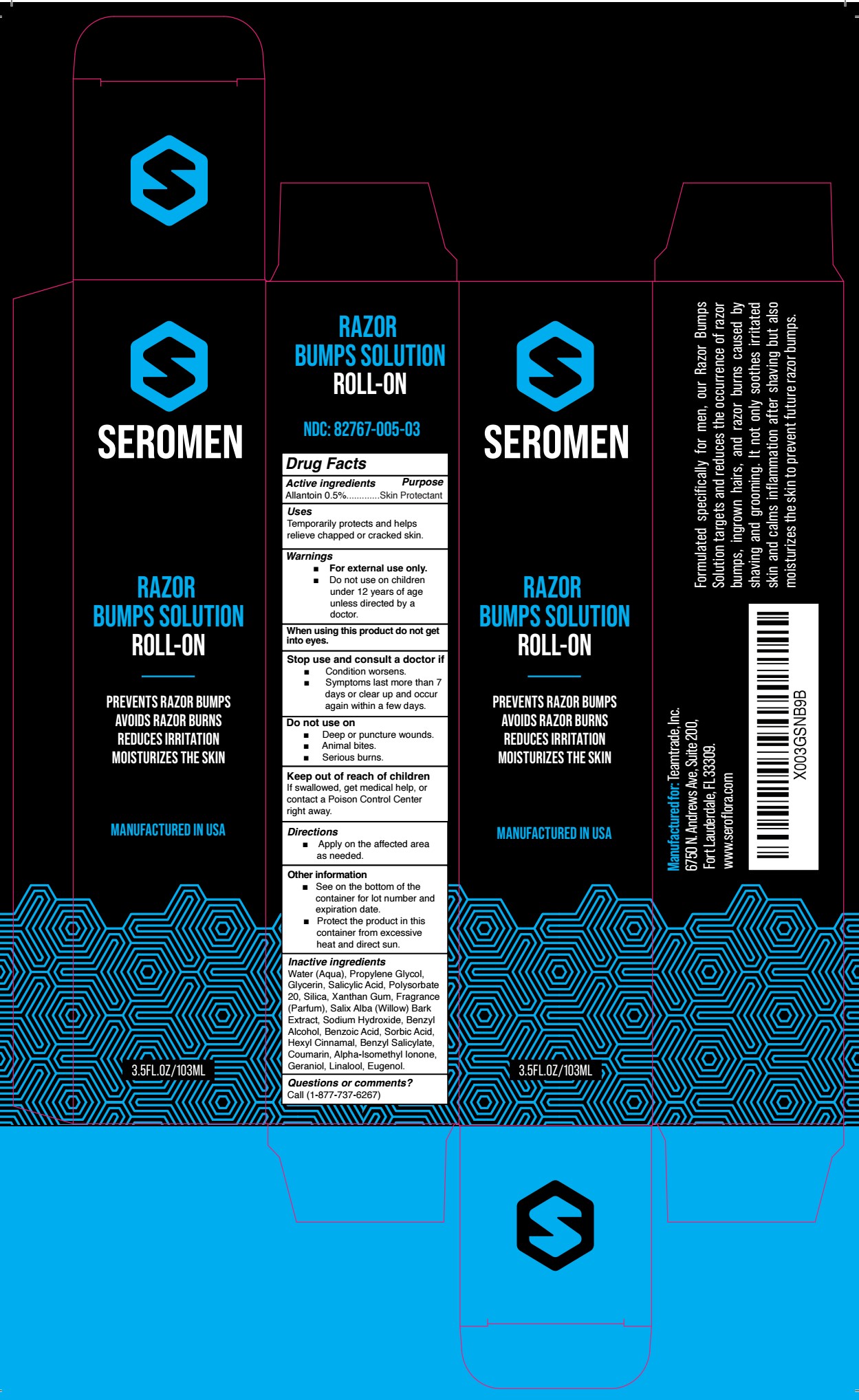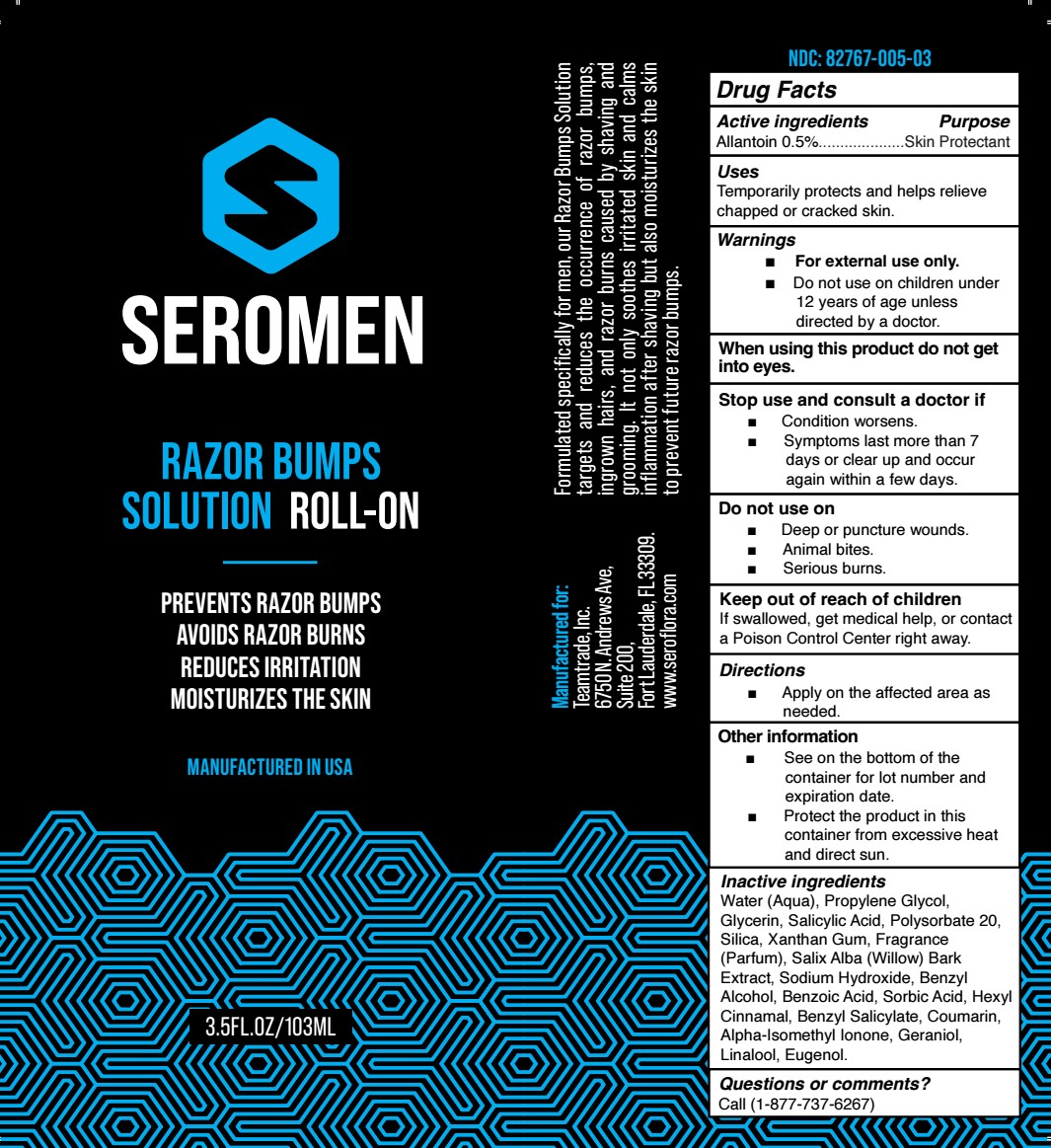 DRUG LABEL: SEROMEN RAZOR BUMPS
NDC: 82767-005 | Form: GEL
Manufacturer: TEAMTRADE INC.
Category: otc | Type: HUMAN OTC DRUG LABEL
Date: 20240610

ACTIVE INGREDIENTS: ALLANTOIN 0.5 g/100 mL
INACTIVE INGREDIENTS: WATER; PROPYLENE GLYCOL; SALICYLIC ACID; POLYSORBATE 20; ISOMETHYL-.ALPHA.-IONONE; LINALOOL, (+/-)-; EUGENOL; BENZOIC ACID; SORBIC ACID; BENZYL ALCOHOL; WILLOW BARK; SODIUM HYDROXIDE; .ALPHA.-HEXYLCINNAMALDEHYDE; BENZYL SALICYLATE; COUMARIN; GERANIOL; GLYCERIN; SILICON DIOXIDE; XANTHAN GUM

82767-005-03

ACTIVE INGREDIENT

Allantoin 0.5%

PURPOSE

Skin Protectant

USE

Temporarily protects and helps relieve chapped or cracked skin.

WARNINGS

For external use only.

Do not use on children under 12 years of age unless directed by a doctor.

WHEN USING

do not get into eyes.

STOP USE

Condition worsens.

Symptoms last more than 7 days or clear up and occur again within a few days.

DO NOT USE

Deep or puncture wounds.
Animal bites.

Serious burns.

KEEP OUT OF REACH OF CHILDREN

If swallowed, get medical help, or contact a Poison Control Center right away.

DIRECTIONS

Apply on the affected area as needed.

OTHER SAFETY INFORMATION

See on the bottom of the container for lot number and expiration date.

Protect the product in this container from excessive heat and direct sun.

INACTIVE INGREDIENT

Water (Aqua), Propylene Glycol, Glycerin, Salicylic Acid, Polysorbate 20, Silica, Xanthan Gum, Fragrance (Parfum), Salix Alba (Willow) Bark Extract, Sodium Hydroxide, Benzyl Alcohol, Benzoic Acid, Sorbic Acid, Hexyl Cinnamal, Benzyl Salicylate, Coumarin, Alpha-Isomethyl Ionone, Geraniol, Linalool, Eugenol.

QUESTIONS OR COMMENTS?

Call (1-877-737-6267)